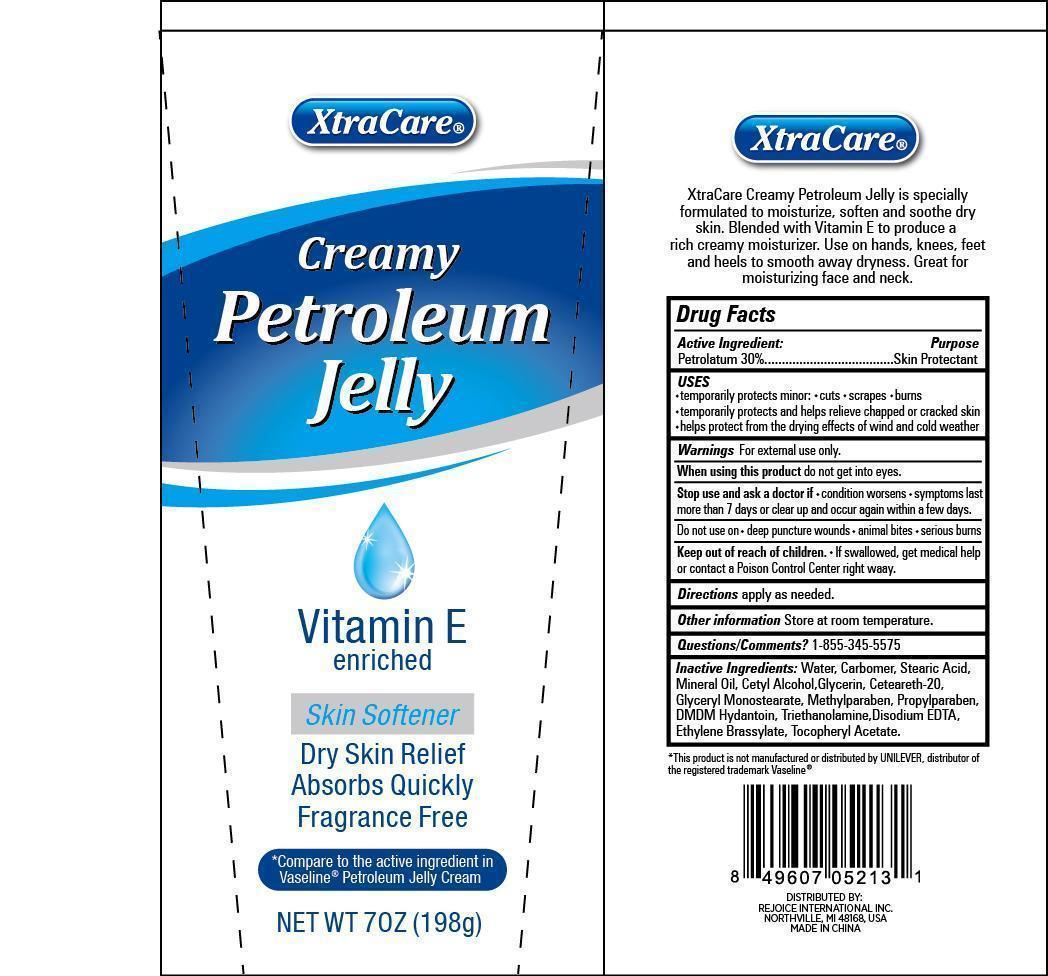 DRUG LABEL: XtraCare Creamy Petroleum Jelly
NDC: 57337-040 | Form: CREAM
Manufacturer: Rejoice International
Category: otc | Type: HUMAN OTC DRUG LABEL
Date: 20240228

ACTIVE INGREDIENTS: PETROLATUM 59 g/198 g
INACTIVE INGREDIENTS: WATER; CARBOMER COPOLYMER TYPE A (ALLYL PENTAERYTHRITOL CROSSLINKED); STEARIC ACID; MINERAL OIL; CETYL ALCOHOL; GLYCERIN; POLYOXYL 20 CETOSTEARYL ETHER; GLYCERYL MONOSTEARATE; METHYLPARABEN; PROPYLPARABEN; DMDM HYDANTOIN; TROLAMINE; EDETATE DISODIUM; .ALPHA.-TOCOPHEROL ACETATE; ETHYLENE BRASSYLATE

XtraCare Creamy Petroleum Jelly

Active Ingredient Purpose

Petrolatum 30% ........................ Skin Protectant

Uses

- temporarily protects minor cuts, scrapes, burns
- temporarily protects and helps relieve chapped or cracked skin
- helps protect from the drying effects of wind and cold weather

Keep out of reach of children. If swallowed, get medical help or contact a Poison Control Center right away.

INDICATIONS AND USAGE

XtraCare® Creamy Petroleum Jelly

Vitamin E enriched

Skin Softener

Dry Skin Relief Absorbs Quickly Fragrance Free

*Compare to the active ingredient in Vaseline® Petroleum Jelly Cream

Net Wt 7oz (198g)

XtraCare®

XtraCare Creamy Petroleum Jelly is specially formulated to moisturize, soften and soothe dry skin. Blended with Vitamin E to product a rich creamy moisturizer. Use on hands, knees, feet and heels to smooth away dryness. Great for moisturizing face and neck.

Warnings

For external use only

When using this productdo not get into eyes.

Stop use and ask a doctor if

- condition worsens
- symptoms last more than 7 days or clear up and occur again within a few days

Do not use on

- deep puncture wounds
- animal bites
- serious burns

DOSAGE AND ADMINISTRATION

Directionsapply as needed.

INACTIVE INGREDIENT

Inactive Ingredients: water, carbomer, stearic acid, mineral oil, cetyl alcohol, glycerin, ceteareth-20, glyceryl monostearate, methylparaben, propylparaben, DMDM hydantoin, triethanolamine, disodium EDTA, ethylene brassylate, tocopheryl acetate

Other informationStore at room temperature.

Questions/Comments? 1-855-345-5575

*This product is not manufactured or distributed by Unilever, distributor of the registered trademark Vaseline ®

DISTRIBUTED BY:

REJOICE INTERNATIONAL INC

NORTHVILLE, MI 48168 USA

MADE IN CHINA